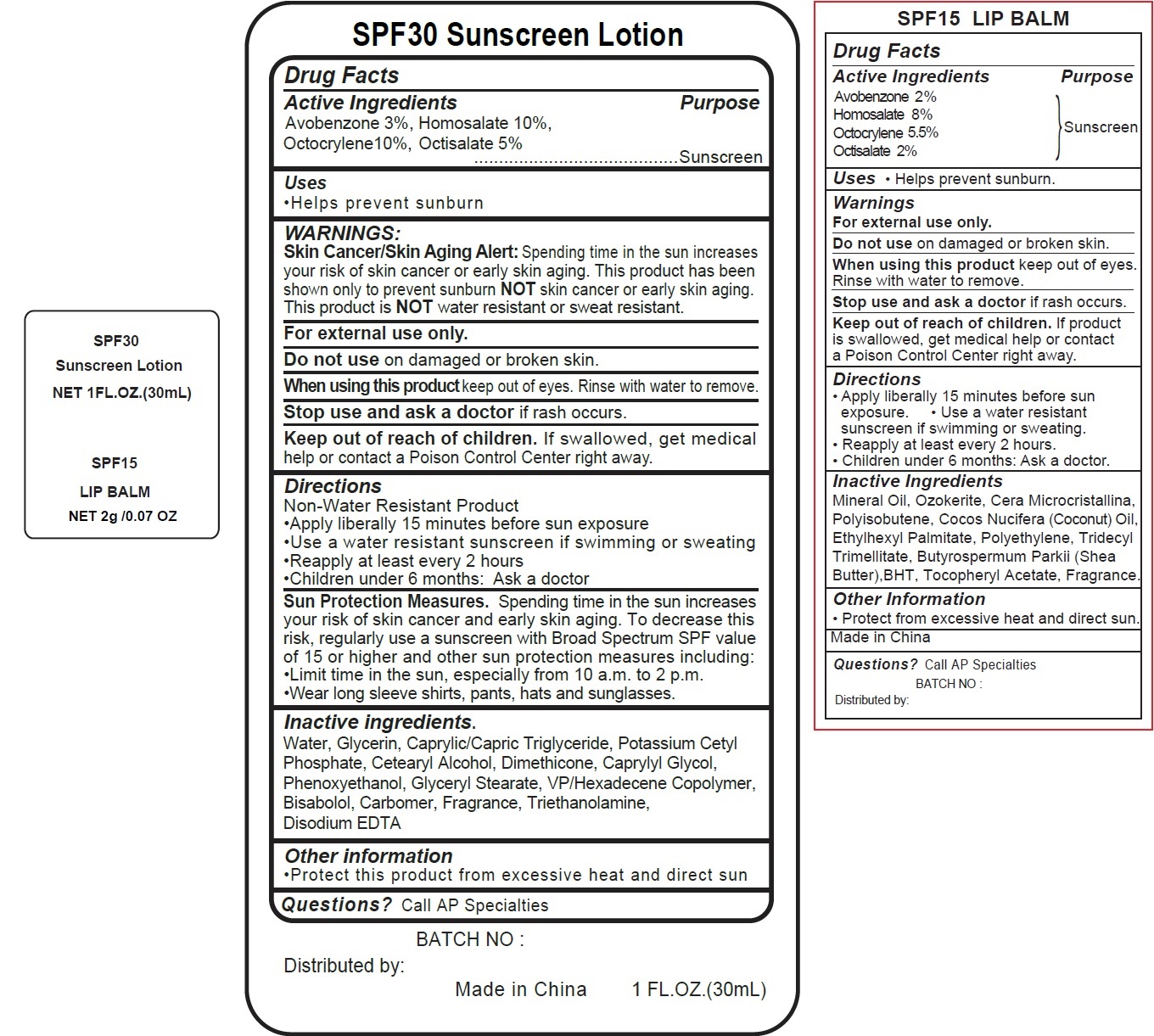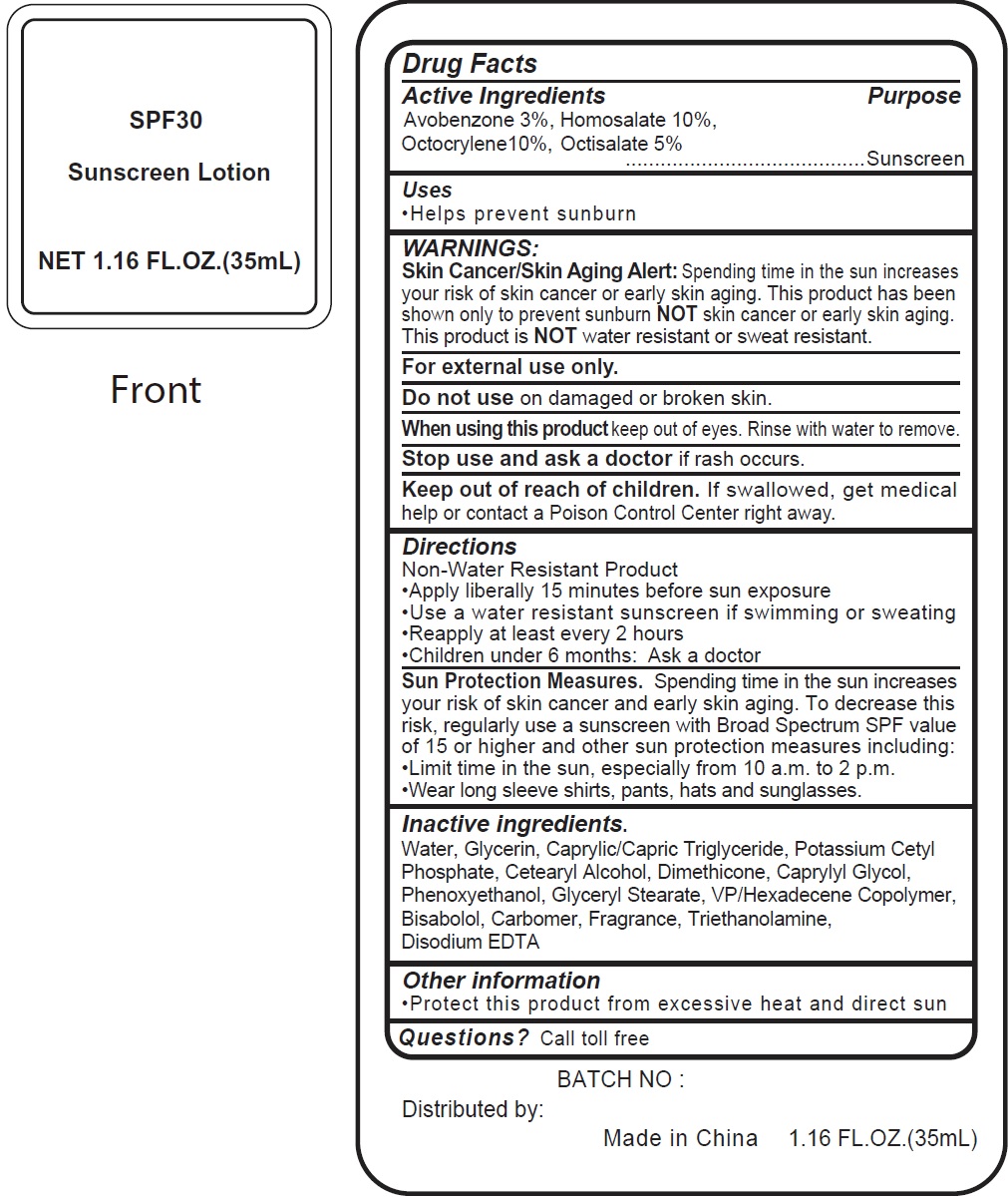 DRUG LABEL: SPF30 Sunscreen and SPF15
NDC: 70412-818 | Form: KIT | Route: TOPICAL
Manufacturer: Zhejiang Ayan Biotech Co.,Ltd.
Category: otc | Type: HUMAN OTC DRUG LABEL
Date: 20231106

ACTIVE INGREDIENTS: AVOBENZONE 30 mg/1 mL; HOMOSALATE 100 mg/1 mL; OCTOCRYLENE 100 mg/1 mL; OCTISALATE 50 mg/1 mL; AVOBENZONE 20 mg/1 g; HOMOSALATE 80 mg/1 g; OCTOCRYLENE 55 mg/1 g; OCTISALATE 20 mg/1 g
INACTIVE INGREDIENTS: CETOSTEARYL ALCOHOL; DIMETHICONE; CAPRYLYL GLYCOL; PHENOXYETHANOL; GLYCERYL MONOSTEARATE; VINYLPYRROLIDONE/HEXADECENE COPOLYMER; LEVOMENOL; CARBOXYPOLYMETHYLENE; TROLAMINE; EDETATE DISODIUM ANHYDROUS; COCONUT; WATER; GLYCERIN; MEDIUM-CHAIN TRIGLYCERIDES; POTASSIUM CETYL PHOSPHATE; MINERAL OIL; CERESIN; COCONUT OIL; ETHYLHEXYL PALMITATE; HIGH DENSITY POLYETHYLENE; TRIDECYL TRIMELLITATE; SHEA BUTTER; BUTYLATED HYDROXYTOLUENE; .ALPHA.-TOCOPHEROL ACETATE

SPF30 Sunscreen Lotion and SPF15 Lip Balm

Active Ingredients

Avobenzone 3%, Homosalate 10%, Octocrylene10%, Octisalate 5%

Purpose

Sunscreen

Uses

•Helps prevent sunburn

WARNINGS:

Spending time in the sun increases your risk of skin cancer or early skin aging. This product has been shown only to prevent sunburn skin cancer or early skin aging. This product is water resistant or sweat resistant. Skin Cancer/Skin Aging Alert: NOTNOT

For external use only.

Do not use

on damaged or broken skin.

When using this product

keep out of eyes. Rinse with water to remove.

Stop use and ask a doctor

if rash occurs.

Keep out of reach of children.

If swallowed, get medical help or contact a Poison Control Center right away.

Directions

Non-Water Resistant Product • Apply liberally 15 minutes before sun exposure • Use a water resistant sunscreen if swimming or sweating • Reapply at least every 2 hours • Children under 6 months: Ask a doctor

Spending time in the sun increases your risk of skin cancer and early skin aging. To decrease this risk, regularly use a sunscreen with Broad Spectrum SPF value of 15 or higher and other sun protection measures including: • Limit time in the sun, especially from 10 a.m. to 2 p.m. • Wear long sleeve shirts, pants, hats and sunglasses. Sun Protection Measures.

Inactive ingredients.

Water, Glycerin, Caprylic/Capric Triglyceride, Potassium Cetyl Phosphate, Cetearyl Alcohol, Dimethicone, Caprylyl Glycol, Phenoxyethanol, Glyceryl Stearate, VP/Hexadecene Copolymer, Bisabolol, Carbomer, Fragrance, Triethanolamine, Disodium EDTA

Other information

• Protect this product from excessive heat and direct sun

Questions?

Call AP Specialties

Active Ingredients

Avobenzone 3%,

Homostate 10%,

Octocrylene 10%,

Octisalate 5%

Purpose

Sunscreen

Uses

- Helps prevent sunburn

WARNINGS

Spending time in the sun increases your risk of skin cnacer or early skin aging. this product has been shown only to prevent sunburn skin cancer or early skin aging. this product is water resistant or sweat resistant. Skin Cancer/Skin Aging Alert: NOTNOT

For external use only.

Do not use

on damaged or broken skin.

When using this product

keep out of eyes. Rinse with water to remove.

Stop use and ask a doctor

if rash occurs.

Keep out of reach of children.

If swallowed, get medical help or contact a Poison Control Center right away.

Directions

- Non-Water Resistant Product
- Apply liberally 15 minutes before sun exposure
- Use a water resistant sunscreen if swimming or sweating
- Reapply at least every 2 hours
- Children under 6 months: Ask a doctor
- Spending time in the sun increases your risk of skin cancer and early skin aging. To decrease this risk, regularly use a sunscreen with Broad Spectrum SPF value of 15 or higher and other sun protection measures including: Sun Protection Measures.

•Limit time in the sun, especially from 10 a.m. to 2 p.m. •Wear long sleeve shirts, pants, hats and sunglasses.

Inactive Ingredients

Water, Glycerin, Caprylic/Capric Triglyceride, Potassium Cetyl Phosphate, Cetearyl Alcohol, Dimethicone, Caprylyl Glycol, Phenoxyethanol, Glyceryl Stearate, VP/Hexadecene Copolymer, Bisabolol, Carbomer, Fragrance, Triethanolamine, Disodium EDTA

Other information

• Protect this product from excessive heat and direct sun

Questions?

Call toll free

Active Ingredients

Avobenzone 2% Octocrylene 8% Octisalate 5.5% Homosalate 2%

Purpose

Sunscreen

Uses

- Helps prevent sunburn.

Warnings

For external use only.

Do not use

on damaged or broken skin.

When using this product

keep out of eyes. Rinse with water to remove.

Stop use and ask a doctor

if reash occurs.

Keep out of reach of children.

If product is swallowed, get medical help or contact a Poison Control right away.

Directions

- Apply liberally 15 minutes before sun exposure.
- Usa a water resistant sunscreen if swimming or sweating.
- Reapply at least every 2 hours.
- Children under 6 months: Ask a doctor.

Inactive Ingredients

Mineral Oil, Ozokerite, Cera Microcristallina, Polyisobutene, Cocos Nucifera (Coconut) Oil, Ethylhexyl Palmitate, Polyethylene, Tridencyl Trimellitate, Butyrospermum Parkii (Shea Butter), BHT, Tocopheryl Acetate, Fragrance.

Other Information

- Protect from excessive heat and direct sun.

Questions?

Call AP Specialties

BATCH NO:

Distributed by: